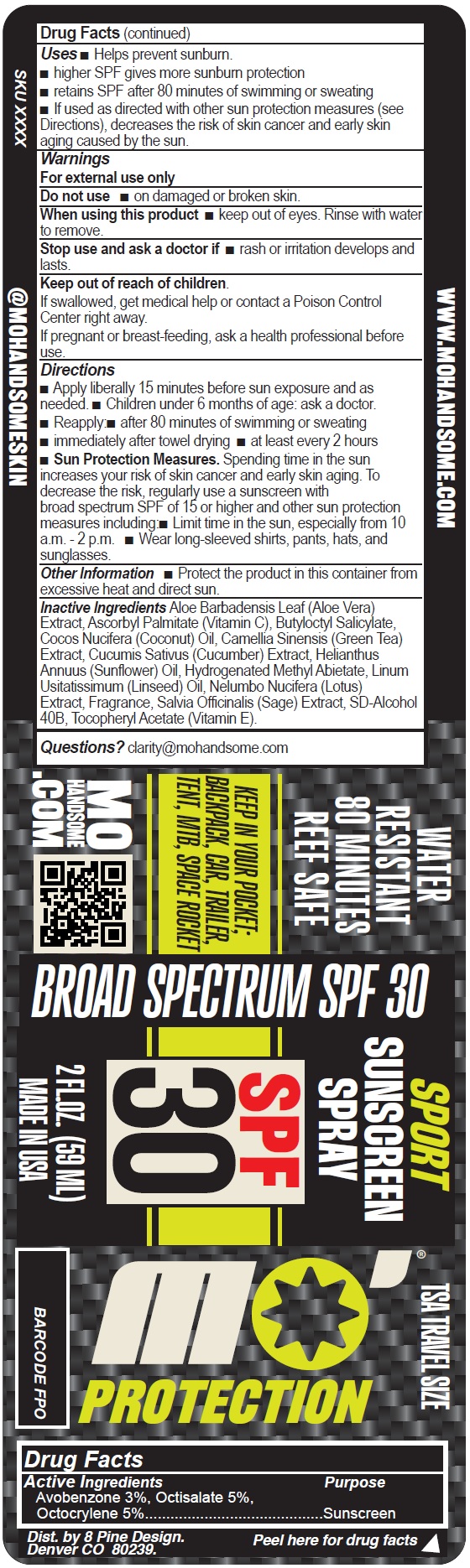 DRUG LABEL: MO HANDSOME Protection Sport Sunscreen SPF 30
NDC: 85932-627 | Form: LIQUID
Manufacturer: 8 PINE DESIGN LLC
Category: otc | Type: HUMAN OTC DRUG LABEL
Date: 20250715

ACTIVE INGREDIENTS: AVOBENZONE 30 mg/1 mL; OCTISALATE 50 mg/1 mL; OCTOCRYLENE 50 mg/1 mL
INACTIVE INGREDIENTS: ALOE VERA LEAF; ASCORBYL PALMITATE; BUTYLOCTYL SALICYLATE; COCONUT OIL; GREEN TEA LEAF; CUCUMBER; HELIANTHUS ANNUUS FLOWERING TOP; HYDROGENATED METHYL ABIETATE; FLAX SEED; CINIDON-ETHYL; SAGE; .ALPHA.-TOCOPHEROL ACETATE

MO HANDSOME Protection Sport Sunscreen SPF 30

Active Ingredients

Avobenzone 3%, Octisalate 5%,
Octocrylene 5%

Purpose

Sunscreen

Uses

- Helps prevent sunburn
- higher SPF gives more sunburn protection
- retains SPF after 80 minutes of swimming or sweating
- If used as directed with other sun protection measures (see Directions), decreases the risk of skin cancer and early skin aging caused by the sun

Warnings

For external use only

Do not use

- on damaged or broken skin

When using this product

- keep out of eyes. Rinse with water to remove.

Stop use and ask a doctor if

- rash or irritation develops and lasts.

Keep out of reach of children.

If swallowed, get medical help or contact a Poison Control Center right away.

If pregnant or breast-feeding

ask a health professional before use.

Directions

- Apply liberally 15 minutes before sun exposure and as needed.
- Children under 6 months of age: ask a docto
- Reapply
- after 80 minutes of swimming or sweating
- immediately after towel drying
- at least every 2 hours
- Sun Protection Measures.Spending time in the sun increases your risk of skin cancer and early skin aging. To decrease the risk, regularly use a sunscreen with broad spectrum SPF of 15 or higher and other sun protection measures including:
- Limit time in the sun, especially from 10 a.m. - 2 p.m.
- Wear long-sleeved shirts, pants, hats, and sunglasses.

Other Information

- Protect the product in this container from excessive heat and direct sun.

Inactive Ingredients

Aloe Barbadensis Leaf (Aloe Vera) Extract, Ascorbyl Palmitate (Vitamin C), Butyloctyl Salicylate, Cocos Nucifera (Coconut) Oil, Camellia Sinensis (Green Tea) Extract, Cucumis Sativus (Cucumber) Extract, Helianthus Annuus (Sunflower) Oil, Hydrogenated Methyl Abietate, Linum Usitatissimum (Linseed) Oil, Nelumbo Nucifera (Lotus) Extract, Fragrance, Salvia Officinalis (Sage) Extract, SD-Alcohol 40B, Tocopheryl Acetate (Vitamin E).

Questions?

clarity@mohandsome.com